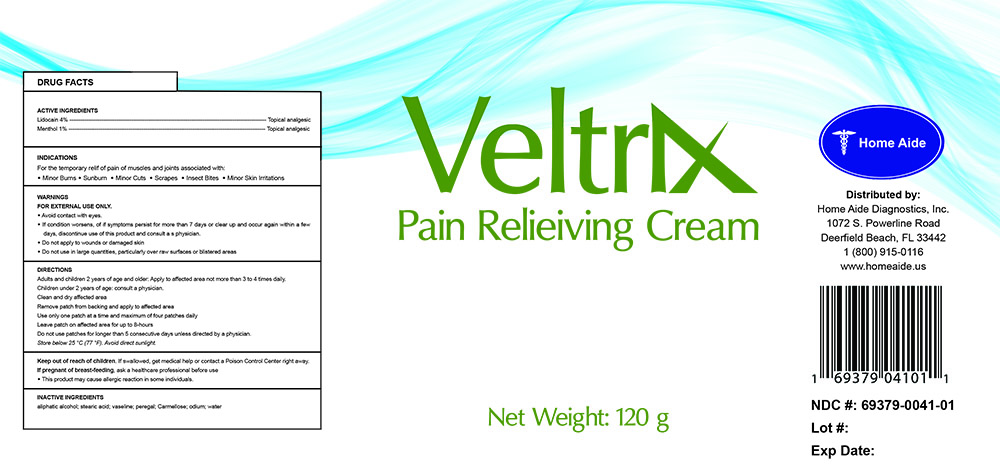 DRUG LABEL: Rematex
NDC: 69379-041 | Form: CREAM
Manufacturer: Home Aide Diagnostics, Inc.
Category: otc | Type: HUMAN OTC DRUG LABEL
Date: 20150630

ACTIVE INGREDIENTS: MENTHOL 1 g/100 g; LIDOCAINE 4 g/100 g
INACTIVE INGREDIENTS: STEARIC ACID

Veltrix Pain Relieiving Cream

ACTIVE INGREDIENTS

Lidocain 4% --------------------------------------------------------------------------------------------------------- Topical analgesic
Menthol 1% --------------------------------------------------------------------------------------------------------- Topical analgesic

PURPOSE

INDICATIONS

For the temporary relif of minor aches and pains of muscles and joints associated with:

- Simple Backache
- Arthritis
- Strains
- Sprains
- Bruises

WARNINGS

FOR EXTERNAL USE ONLY.

- Avoid contact with eyes.
- If condition worsens, of if symptoms persist for more than 7 days or clear up and occur again within a few days, discontinue use of this product and consult a s physician.
- Do not apply to wounds or damaged skin
- Do not bandage tightly

DIRECTIONS

- Clean and dry affected area
- Remove patch from backing and apply to affected area
- Use only one patch at a time and maximum of four patches daily
- Leave patch on affected area for up to 8-hours
- Do not use patches for longer than 5 consecutive days unless directed by a physician.
- Store below 25 °C (77 °F). Avoid direct sunlight.

Keep out of reach of children. If swallowed, get medical help or contact a Poison Control Center right away.

PREGNANCY OR BREAST FEEDING

If pregnant of breast-feeding, ask a healthcare professional before use

- This product may cause allergic reaction in some individuals.

INACTIVE INGREDIENTS

aliphatic alcohol; stearic acid; vaseline; peregal; Carmellose Sodium; water;

INDICATIONS AND USAGE

- Adults and children 2 years of age and older: Apply to affected area not more than 3 to 4 times daily.
- Children under 2 years of age: consult a physician.